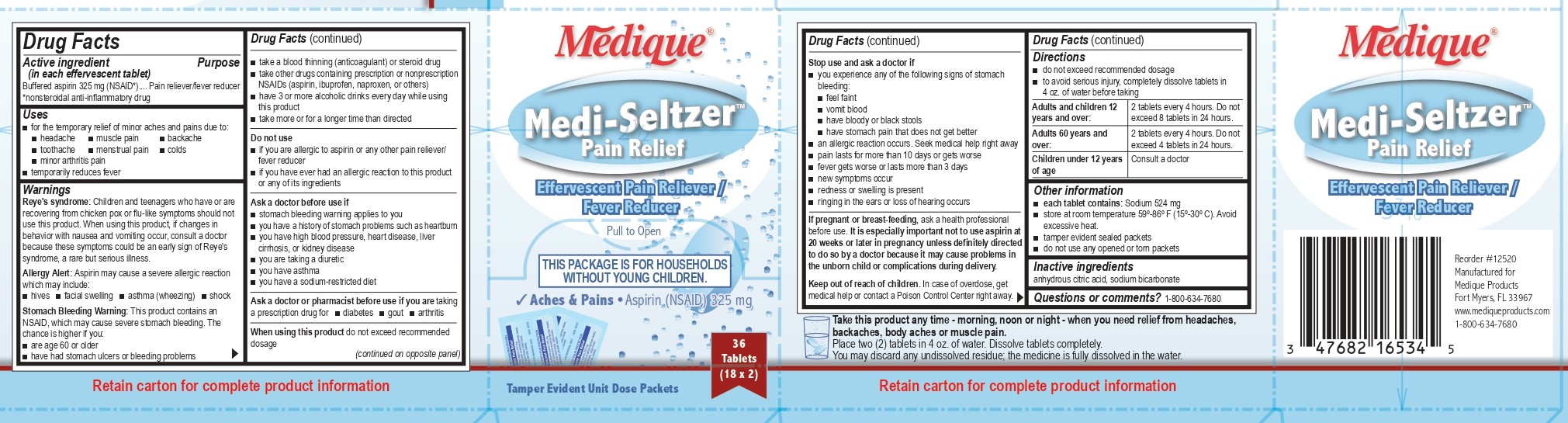 DRUG LABEL: Medique Medi-Seltzer Pain Relief
NDC: 47682-147 | Form: TABLET, EFFERVESCENT
Manufacturer: Unifirst First Aid Corporation
Category: otc | Type: HUMAN OTC DRUG LABEL
Date: 20250908

ACTIVE INGREDIENTS: ASPIRIN 325 mg/1 1
INACTIVE INGREDIENTS: CITRIC ACID MONOHYDRATE; SODIUM BICARBONATE

Medique Medi-Seltzer Pain Relief

Drug Facts

Active Ingredients (in each effervescent tablet)

Buffered aspirin 325 mg (NSAID)*

*nonsteroidal anti-inflammatory drug

Purpose

Pain Reliever / Fever Reducer

Uses

- for the temporary relief of minor aches and pains due to:
- headache
- muscle pain
- backache
- toothache
- menstrual pain
- colds
- minor arthritis pain
- temporarily reduces fever

Warnings

Reye's syndrome: Children and teenagers who have or are recovering from chicken pox or flu-like symptoms should not use this product. When using this product, if changes in behavior with nausea and vomiting occur, consult a doctor because these symptoms could be an early sign of Reye's syndrome, a rare but serious illness.

Allergy Alert: Aspirin may cause a severe allergic reaction which may include:

hives
facial swelling
asthma (wheezing)
shock

Stomach bleeding warning: This product contains an NSAID, which may cause severe stomach bleeding. The chance is higher if you:

are age 60 or older
have had stomach ulcers or bleeding problems
take a blood thinning (anticoagulant) or steroid drug
take other drugs containing prescription or nonprescription NSAIDs (aspirin, ibuprofen, naproxen, or others)
have 3 or more alcoholic drinks every day while using this product
take more or for a longer time than directed

Do not use

- if you are allergic to aspirin or any other pain reliever/ fever reducer
- if you have ever had an allergic reaction to this product or any of its ingredients

Ask a doctor before use if

- stomach bleeding warning applies to you
- you have a history of stomach problems such as heartburn
- you have high blood pressure, heart disease, liver cirrhosis, or kidney disease
- you are taking a diuretic
- you have asthma
- you have a sodium-restricted diet

Ask a doctor or pharmacist before use if you are taking a prescription drug for:

- diabetes
- gout
- arthritis

When using this product do not take exceed recommended dosage

Stop use and ask a doctor if

- you experience any of the following signs of stomach bleeding
- you feel faint
- vomit blood
- have bloody or black stools
- have stomach pain that does not get better
- an allergic reaction occurs. Seek medical help right away
- pain lasts for more than 10 days or gets worse
- fever gets worse or lasts more than 3 days
- new symptoms appear
- redness or swelling is present
- ringing in the ears or a loss of hearing occurs

PREGNANCY OR BREAST FEEDING

If pregnant or breast-feeding, ask a health professional before use. It is especially important not to use aspirin at 20 weeks or later in pregnancy, unless definitely directed to do so by a doctor because it may cause problems in the unborn child or complications during delivery.

Keep out of reach of children. In case of overdose, get medical help or contact a Poison Control Center right away.

Directions

- do not exceed recommended dosage
- to avoid serious injury, completely dissolve tablets in 4 oz. of water before taking.

Adults and children 12 years and over:

2 tablets every 4 hours, or as directed by a doctor. Do not exceed 8 tablets in 24 hours

Adults 60 years and over:

2 tablets every 4 hours, or as directed by a doctor. Do not exceed 4 tablets in 24 hours

Children under 12 years of age:

Consult a doctor

Other information

- each tablet contains: Sodium 524mg
- store at room temperature 59º-86º F (15º-30º C) avoid excessive heat.
- tamper evident sealed packets
- do not use any opened or torn packets

Inactive ingredients: anhydrous citric acid, sodium bicarbonate

Questions or comments? 1-800-634-7680

PACKAGE LABEL

Medique®

Medi-Seltzer

Pain Relief

Effervescent Antacid / Pain Reliever

Pull to Open

This Package is for Households without Young Children.

Aches, Fever ● Aspirin (NSAID) 325 mg

Antacid ● Citric Acid 1000 mg Sodium Bicarbonate 1916 mg

36 Tablets

(18 x 2)

Tamper Evident Unit Dose Packets